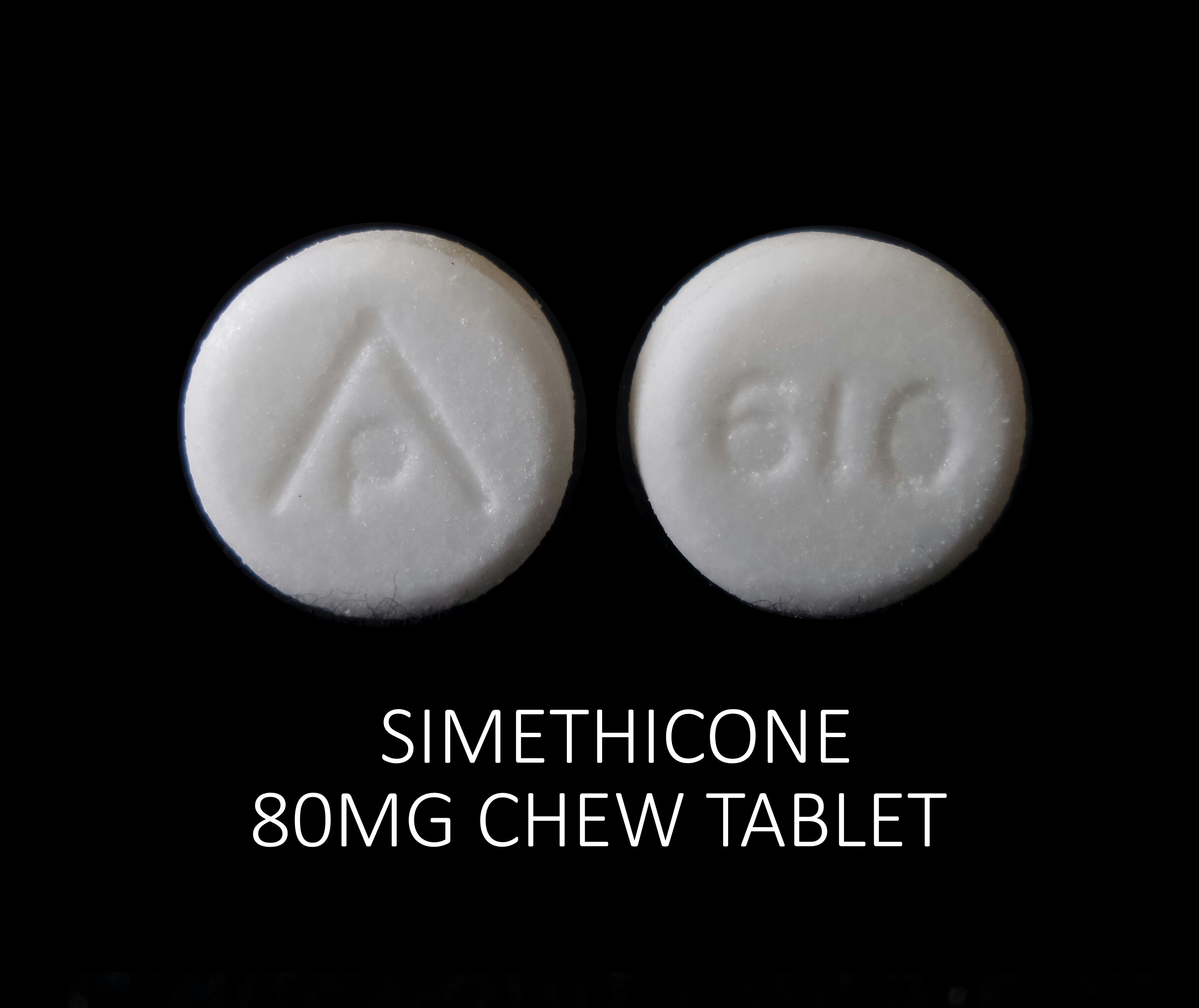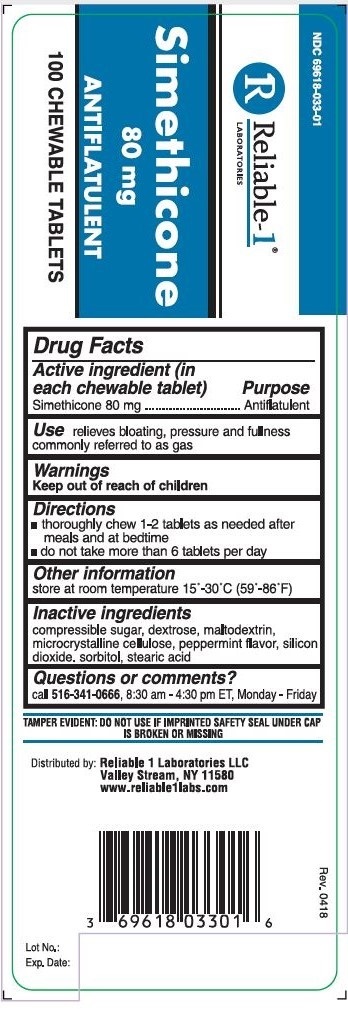 DRUG LABEL: Simethicone 80 mg
NDC: 69618-033 | Form: TABLET, CHEWABLE
Manufacturer: Reliable 1 Laboratories LLC
Category: otc | Type: HUMAN OTC DRUG LABEL
Date: 20250115

ACTIVE INGREDIENTS: DIMETHICONE 80 mg/1 1
INACTIVE INGREDIENTS: CELLULOSE, MICROCRYSTALLINE; SILICON DIOXIDE; MALTODEXTRIN; SORBITOL; STEARIC ACID; SUCROSE; DEXTROSE; PEPPERMINT

Simethicone 80 mg

Drug Facts

Use

relieves bloating, pressure and fullness commonly referred to as gas

Warnings

Keep out of reach of children

Keep out of reach of children

Directions

- thoroughly chew 1-2 tablets as needed after meals and at bedtime
- do not take more then 6 tablets per day

Other information

store at room temperature 15°-30°C (59°-86°F)

Inactive ingredients

compressible sugar, dextrose, maltodextrin, micdocrystalline cellulose, peppermint flavor, Silicon dioxide, sorbitol, stearic acid

Questions or comments?

call 516-341-0666, 8:30 am to 4:30 pm ET, Monday - Friday

TAMPER EVIDENT: DO NOT USE IF IMPRINTED SAFETY SEAL UNDER CAP IS BROKEN OR MISSING

Distributed by: Reliable 1 Laboratories LLC

Valley Stream, NY 11580

www.reliable1labs.com

Active ingredient (in each chewable tablet)

Simethicone 80 mg

Purpose

Antiflatulent

PACKAGE LABEL

NDC 69618-033-01

Simethicone 80 mg

ANTIFLATULENT

100 CHEWABLE TABLETS